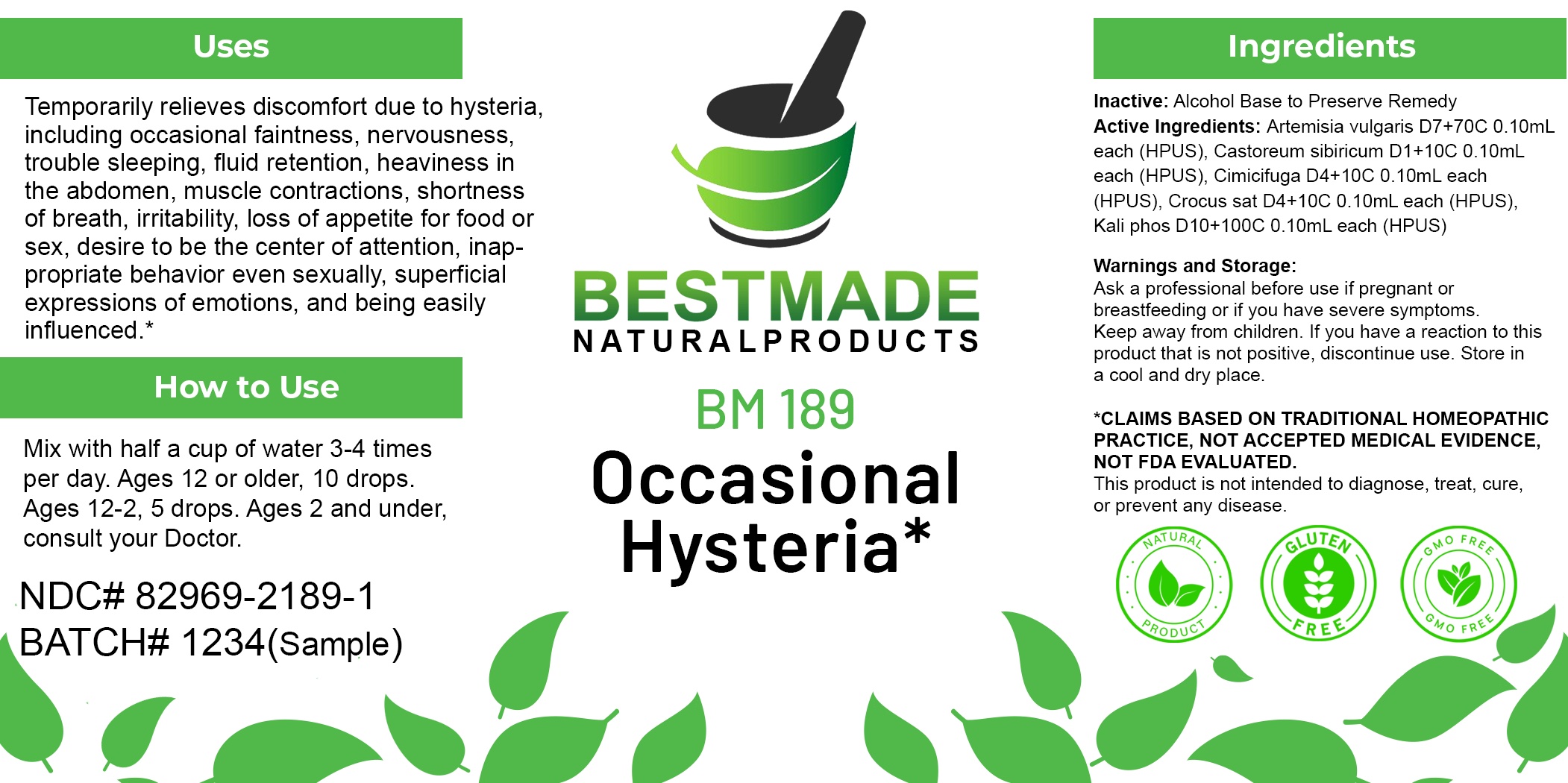 DRUG LABEL: Bestmade Natural Products BM189
NDC: 82969-2189 | Form: LIQUID
Manufacturer: Bestmade Natural Products
Category: homeopathic | Type: HUMAN OTC DRUG LABEL
Date: 20250221

ACTIVE INGREDIENTS: POTASSIUM PHOSPHATE, UNSPECIFIED FORM 30 [hp_C]/30 [hp_C]; ARTEMISIA VULGARIS ROOT 30 [hp_C]/30 [hp_C]; SAFFRON 30 [hp_C]/30 [hp_C]; CASTOR CANADENSIS SCENT GLAND SECRETION 30 [hp_C]/30 [hp_C]; BLACK COHOSH 30 [hp_C]/30 [hp_C]
INACTIVE INGREDIENTS: ALCOHOL 30 [hp_C]/30 [hp_C]

BM189

DOSAGE AND ADMINISTRATION

How to Use

Mix with half a cup of water 3-4 times per day. Ages 12 or older, 10 drops. Ages 12-2, 5 drops. Ages 2 and under, consult your Doctor.

Inactive:

Alcohol Base to Preserve Product

ACTIVE INGREDIENTS

Artemisia vulgaris D7+70C 0.10mL each (HPUS), Castoreum sibiricum D1+10C 0.10mL each (HPUS), Cimicifuga D4+10C 0.10mL each (HPUS), Crocus sat D4+10C 0.10mL each (HPUS), Kali phos D10+100C 0.10mL each (HPUS)

KEEP OUT OF REACH OF CHILDREN

Warnings and Storage:

Ask a professional before use if pregnant or breastfeeding or if you have severe symptoms.

Keep away from children. If you have a reaction to this product that is not positive, discontinue use. Store in a cool and dry place

*CLAIMS BASED ON TRADITIONAL HOMEOPATHIC PRACTICE, NOT ACCEPTED MEDICAL EVIDENCE NOT FDA EVALUATED.
This product is not intended to diagnose, treat, cure, or prevent any disease.

Warnings and Storage:

Ask a professional before use if pregnant or breastfeeding or if you have severe symptoms.

Keep away from children. If you have a reaction to this product that is not positive, discontinue use. Store in a cool and dry place

*CLAIMS BASED ON TRADITIONAL HOMEOPATHIC PRACTICE, NOT ACCEPTED MEDICAL EVIDENCE NOT FDA EVALUATED.
This product is not intended to diagnose, treat, cure, or prevent any disease.

Uses
Temporarily relieves discomfort due to hysteria, including occasional faintness, nervousness, trouble sleeping, fluid retention, heaviness in the abdomen, muscle contractions, shortness of breath, irritability, loss of appetite for food or sex, desire to be the center of attention, inappropriate behavior even sexually, superficial expressions of emotions, and being easily influenced.*

Uses
Temporarily relieves discomfort due to hysteria, including occasional faintness, nervousness, trouble sleeping, fluid retention, heaviness in the abdomen, muscle contractions, shortness of breath, irritability, loss of appetite for food or sex, desire to be the center of attention, inappropriate behavior even sexually, superficial expressions of emotions, and being easily influenced.*

Entire package label